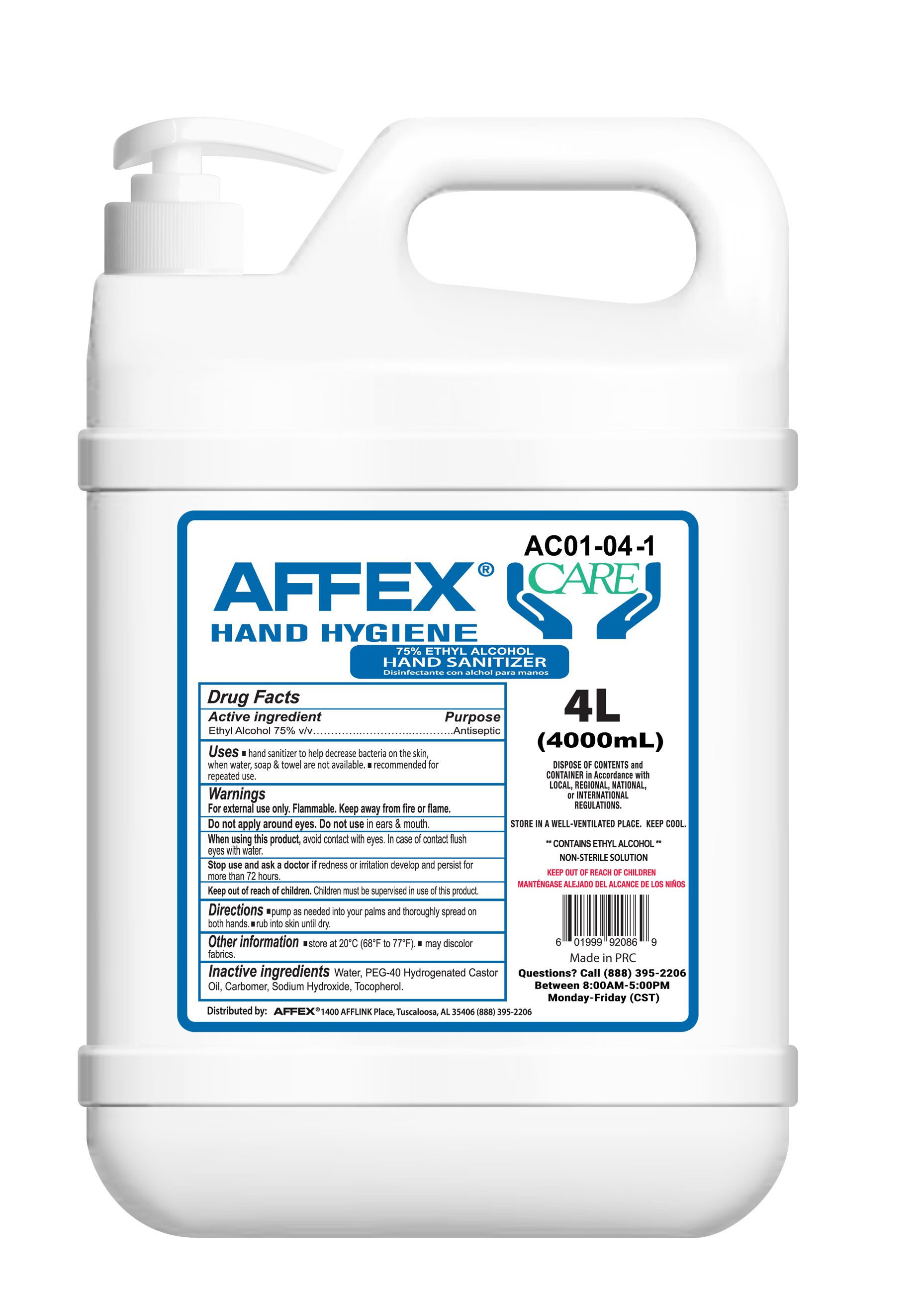 DRUG LABEL: Focan LLC AFFEX CARE Hand Sanitizer(AC01-04-01)
NDC: 74913-555 | Form: GEL
Manufacturer: SHANTOU S.E.Z BAOJIE INDUSTRY CO., LTD
Category: otc | Type: HUMAN OTC DRUG LABEL
Date: 20200613

ACTIVE INGREDIENTS: ALCOHOL 75 mL/100 mL
INACTIVE INGREDIENTS: PEG-40 CASTOR OIL 0.5 mL/100 mL; CARBOMER 940 0.5 mL/100 mL; WATER 23.2 mL/100 mL; TOCOPHEROL 0.5 mL/100 mL; SODIUM HYDROXIDE 0.3 mL/100 mL

Focan LLC Affex Care Hand Sanitizer

active ingredients

Alcohol :62% v/v. Purpose: Antiseptic

Antiseptic

hand sanitizer

use

Hand sanitizer to help reduce bacteria that potentially can cause disease. For use when soap and water are not available

Warnings

For external use only. Flammable. Keep away from heat or flame

Do note use

In children less than 2 months of age. On open skin wounds

When using this product keep out of eyes ears and mouth. In case of contact with eyes rinse eyes throughly with water

Stop use and ask a doctor if irritation or rash occurs. These may be signs of a serious condition.

keep out of reach of children. If swalloed get medical help or contact a poison control center right away

Direction

Place enought product on hands to cover all surfaces.Rub hands together until dry.

Supervise children under 6 years of age when using this product to avoid swallowing.

Other information

Store between 15-30C (59-86F)

Avoid freezing and excessive heat above 40C(104F)

Inactive ingredients

Water, Peg-40 Castor oil, Carbomer ,sodium hydroxide ,Tocopherol